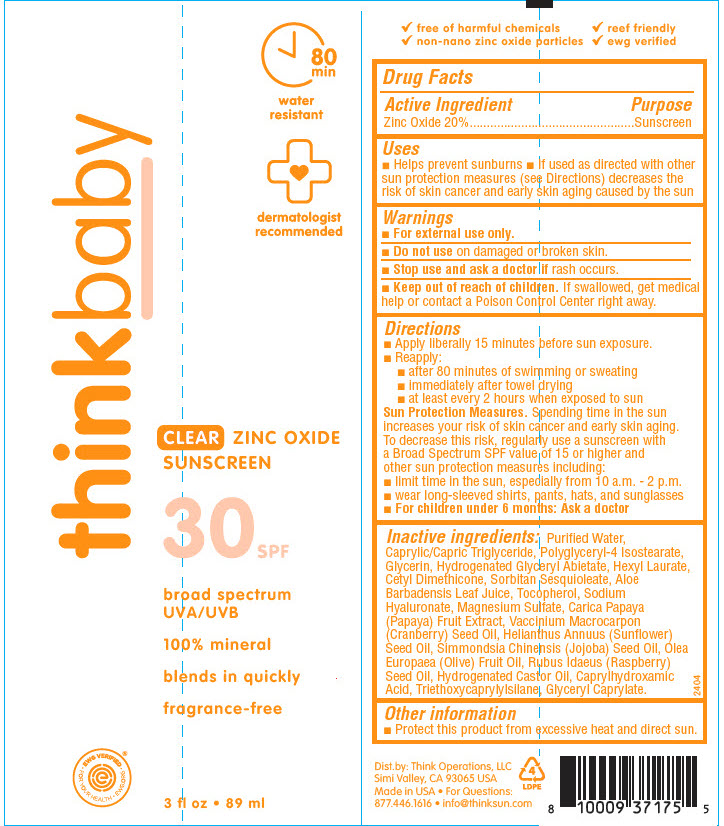 DRUG LABEL: Thinkbaby Clear Zinc 
NDC: 60781-4175 | Form: LOTION
Manufacturer: thinkOperations,LLC
Category: otc | Type: HUMAN OTC DRUG LABEL
Date: 20240724

ACTIVE INGREDIENTS: ZINC OXIDE 200 mg/1 mL
INACTIVE INGREDIENTS: WATER; MEDIUM-CHAIN TRIGLYCERIDES; POLYGLYCERYL-4 ISOSTEARATE; GLYCERIN; GLYCERYL ABIETATE; HEXYL LAURATE; CETYL DIMETHICONE 150; SORBITAN SESQUIOLEATE; ALOE VERA LEAF; .ALPHA.-TOCOPHEROL; HYALURONATE SODIUM; BISPYRITHIONE MAGSULFEX ANHYDROUS; PAPAYA; CRANBERRY SEED OIL; SUNFLOWER OIL; JOJOBA OIL; OLIVE OIL; RASPBERRY SEED OIL; HYDROGENATED CASTOR OIL; CAPRYLHYDROXAMIC ACID; TRIETHOXYCAPRYLYLSILANE; GLYCERYL MONOCAPRYLATE

Thinkbaby Clear Zinc
SPF 30

Drug Facts

Active Ingredient

Zinc Oxide 20%

Purpose

Sunscreen

Uses

- Helps prevent sunburns
- If used as directed with other sun protection measures (see Directions) decreases the risk of skin cancer and early skin aging caused by the sun

Warnings

- For external use only.

- Do not use on damaged or broken skin.

- Stop use and ask a doctor if rash occurs.

- Keep out of reach of children. If swallowed, get medical help or contact a Poison Control Center right away.

Directions

- Apply liberally 15 minutes before sun exposure.
- Reapply:
  - after 80 minutes of swimming or sweating
  - immediately after towel drying
  - at least every 2 hours when exposed to sun

Sun Protection Measures. Spending time in the sun increases your risk of skin cancer and early skin aging. To decrease this risk, regularly use a sunscreen with a Broad Spectrum SPF value of 15 or higher and other sun protection measures including:

- limit time in the sun, especially from 10 a.m. - 2 p.m.
- wear long-sleeved shirts, pants, hats, and sunglasses
- For children under 6 months: Ask a doctor

Inactive ingredients

Purified Water, Caprylic/Capric Triglyceride, Polyglyceryl-4 Isostearate, Glycerin, Hydrogenated Glyceryl Abietate, Hexyl Laurate, Cetyl Dimethicone, Sorbitan Sesquioleate, Aloe Barbadensis Leaf Juice, Tocopherol, Sodium Hyaluronate, Magnesium Sulfate, Carica Papaya (Papaya) Fruit Extract, Vaccinium Macrocarpon (Cranberry) Seed Oil, Helianthus Annuus (Sunflower) Seed Oil, Simmondsia Chinensis (Jojoba) Seed Oil, Olea Europaea (Olive) Fruit Oil, Rubus Idaeus (Raspberry) Seed Oil, Hydrogenated Castor Oil, Caprylhydroxamic Acid, Triethoxycaprylylsilane, Glyceryl Caprylate.

Other information

- Protect this product from excessive heat and direct sun.

For Questions

877.446.1616

Dist.by: Think Operations, LLC
Simi Valley, CA 93065 USA

PRINCIPAL DISPLAY PANEL - 89 ml Tube Label

thinkbaby

80
min

water
resistant

dermatologist
recommended

CLEAR ZINC OXIDE
SUNSCREEN

30 SPF

broad spectrum
UVA/UVB

100% mineral

blends in quickly

fragrance-free

• EWG VERIFIED •
FOR YOUR HEALTH • EWG.ORG

3 fl oz • 89 ml